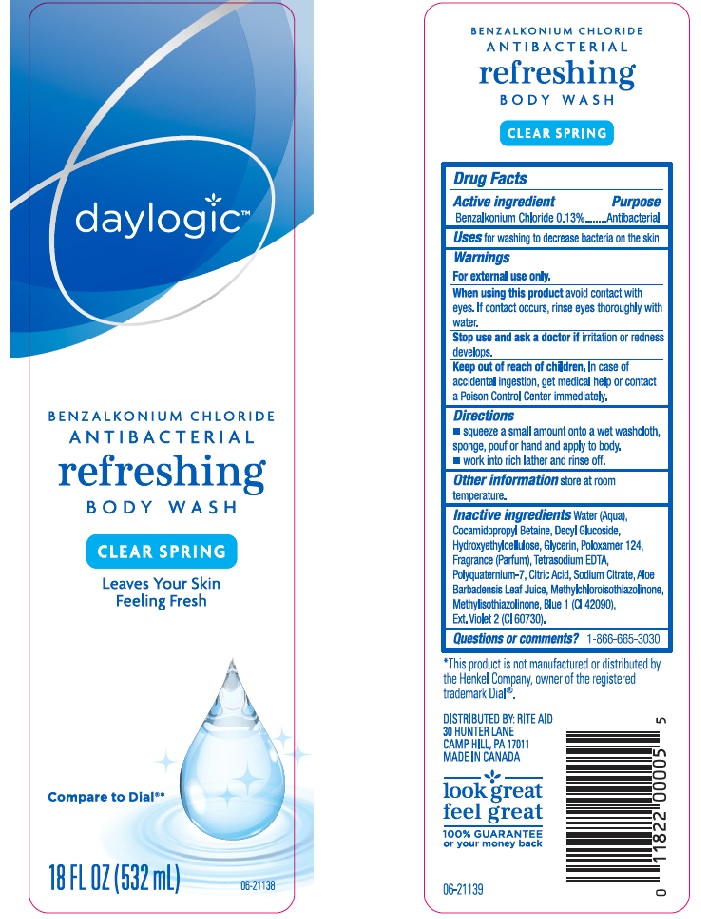 DRUG LABEL: Daylogic Refreshing Body Wash
NDC: 11822-8151 | Form: LIQUID
Manufacturer: Rite Aid Corporation
Category: otc | Type: HUMAN OTC DRUG LABEL
Date: 20160808

ACTIVE INGREDIENTS: BENZALKONIUM CHLORIDE 1.3 mg/1 mL
INACTIVE INGREDIENTS: WATER; COCAMIDOPROPYL BETAINE; DECYL GLUCOSIDE; HYDROXYETHYL CELLULOSE (5000 CPS AT 1%); GLYCERIN; POLOXAMER 124; EDETATE SODIUM; POLYQUATERNIUM-7 (70/30 ACRYLAMIDE/DADMAC; 1600000 MW); CITRIC ACID MONOHYDRATE; SODIUM CITRATE; ALOE VERA LEAF; METHYLCHLOROISOTHIAZOLINONE; METHYLISOTHIAZOLINONE; FD&C BLUE NO. 1; EXT. D&C VIOLET NO. 2

DRUG FACTS

Active ingredient

Benzalkonium chloride 0.13%

Purpose

Antibacterial

Uses

for washing to decrease bacteria on the skin.

Warnings

For external use only.

When using this product

avoid contact with eyes. If contact occurs, rinse eyes thoroughly with water.

Stop use and ask a doctor if

irritation or redness develops.

Keep out of reach of children.

In case of accidental ingestion, get medical help or contact a Poison Control Center immediately.

Directions

- Squeeze a small amount onto a wet washcloth, sponge, pouf or hand and apply to body.
- work into rich lather and rinse off.

Other information

store at room temperature.

Inactive ingredients

Water (Aqua), Cocamidopropyl Betaine, Decyl Glucoside, Hydroxyethylcellulose, Glycerin, Poloxamer 124, Fragrance (Parfum), Tetrasodium EDTA, Polyquaternium-7, Citric Acid, Sodium Citrate, Aloe Barbadensis Leaf Juice, Methylchloroisothiazolinone, Methylisothiazolinone, Blue 1 (CI 42090), Ext. Violet 2 (CI 60730).

Questions or comments?

1-866-665-3030